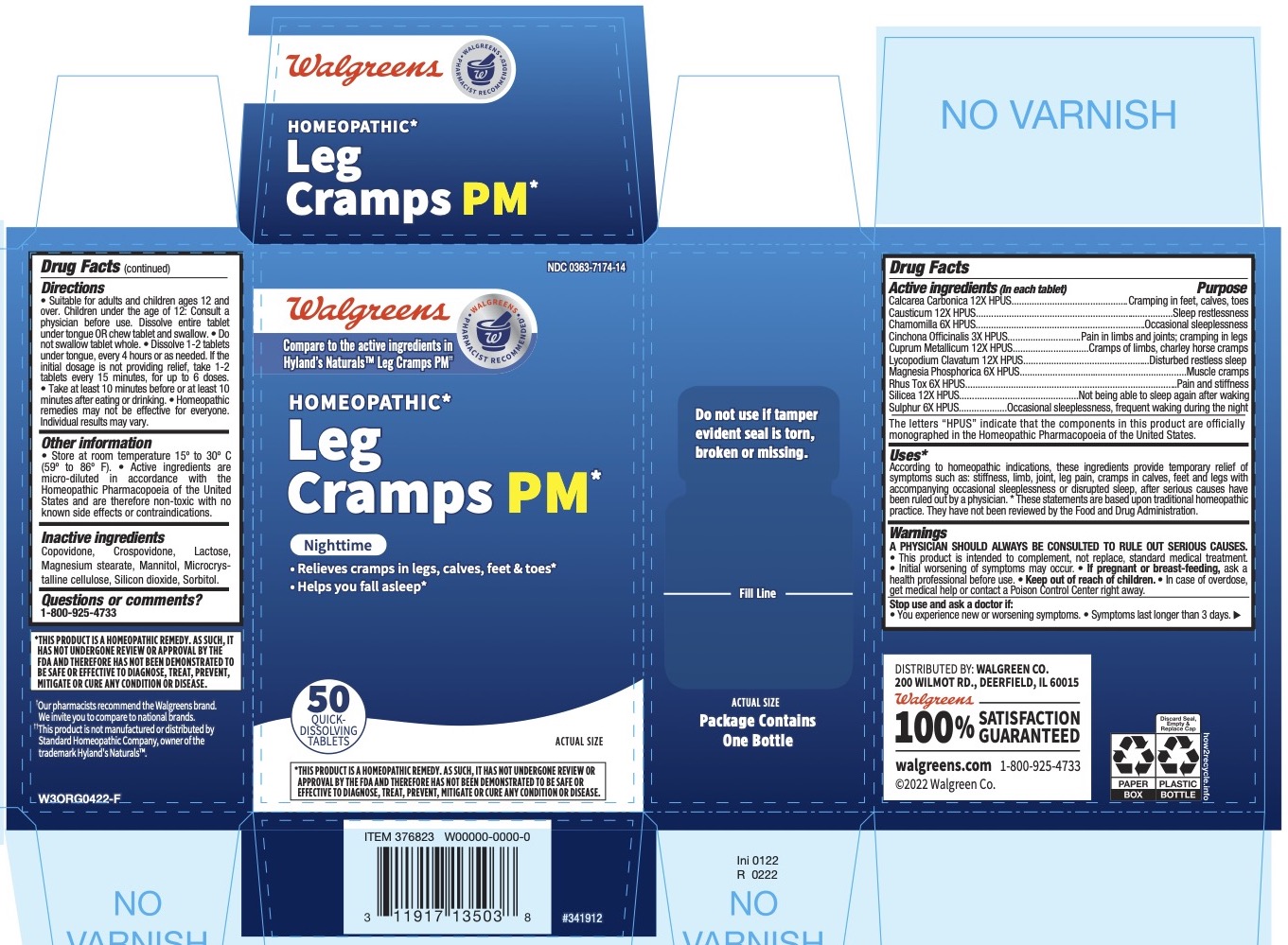 DRUG LABEL: LEG CRAMPS PM
NDC: 0363-7174 | Form: TABLET
Manufacturer: Walgreen Company
Category: homeopathic | Type: HUMAN OTC DRUG LABEL
Date: 20251217

ACTIVE INGREDIENTS: CINCHONA OFFICINALIS BARK 3 [hp_X]/1 1; MATRICARIA RECUTITA 6 [hp_X]/1 1; LYCOPODIUM CLAVATUM SPORE 12 [hp_X]/1 1; SILICON DIOXIDE 12 [hp_X]/1 1; SULFUR 6 [hp_X]/1 1; COPPER 12 [hp_X]/1 1; CAUSTICUM 12 [hp_X]/1 1; TOXICODENDRON PUBESCENS LEAF 6 [hp_X]/1 1; MAGNESIUM PHOSPHATE, DIBASIC TRIHYDRATE 6 [hp_X]/1 1; OYSTER SHELL CALCIUM CARBONATE, CRUDE 12 [hp_X]/1 1
INACTIVE INGREDIENTS: COPOVIDONE K25-31; MAGNESIUM STEARATE; MANNITOL; MICROCRYSTALLINE CELLULOSE; LACTOSE MONOHYDRATE; CROSPOVIDONE; SORBITOL

Walgreens Leg Cramps PM 50 Tablets

PURPOSE

According to homeopathic indications, these ingredients provide temporary relief of symptoms such as: stiffness, limb, joint, leg pain, cramps in calves, feet and legs with accompanying occasional sleeplessness or disrupted sleep, after serious causes have been ruled out by a physician.

Drug Facts

Active ingredients

Active ingredients |  | Purpose
Calcarea Carbonica 12X HPUS |  | cramps in legs, calves, feet and toes
Causticum 12X HPUS |  | occasional sleeplessness
Chamomilla 6X HPUS |  | occasional sleeplessness
Cinchona Officinalis 3X HPUS |  | pain in limbs and joints; cramping in legs
Cuprum Metallicum 12X HPUS |  | cramps of limbs, charley horse cramps
Lycopodium 12X HPUS |  | disturbed, restless sleep
Magnesia Phosphorica 6X HPUS |  | muscle cramps
Rhus Toxicodendron 6X HPUS |  | pain and stiffness
Silicea 12X HPUS |  | not being able to sleep again after waking
Sulphur 6X HPUS |  | occasional sleeplessness, frequent waking during night

“HPUS” indicates that the active ingredients are in the official Homeopathic Pharmacopœia of the United States.

Uses

■ According to homeopathic indications, these ingredients provide temporary relief of symptoms such as: stiffness, limb, joint, leg pain, cramps in calves, feet and legs with accompanying occasional sleeplessness or disrupted sleep, after serious causes have been ruled out by a physician. * These statements are based upon traditional homeopathic practice. They have not been reviewed by the Food and Drug Administration.

Warnings

A PHYSICIAN SHOULD ALWAYS BE CONSULTED TO RULE OUT SERIOUS CAUSES.

• This product is intended to complement, not replace, standard medical treatment. • Initial worsening of symptoms may occur.

PREGNANCY OR BREAST FEEDING

• If pregnant or breast-feeding, ask a health professional before use.

Stop use and ask a doctor if:

• You experience new or worsening symptoms. • Symptoms last longer than 3 days.

• Keep out of reach of children. • In case of overdose, get medical help or contact a Poison Control Center right away.

Drug Facts(continued)

Directions

• Suitable for adults and children ages 12 and over. Children under the age of 12: Consult a physician before use. Dissolve entire tablet under tongue OR chew tablet and swallow. • Do not swallow tablet whole. • Dissolve 1-2 tablets under tongue, every 4 hours or as needed. If the initial dosage is not providing relief, take 1-2 tablets every 15 minutes, for up to 6 doses. • Take at least 10 minutes before or at least 10 minutes after eating or drinking. • Homeopathic remedies may not be effective for everyone. Individual results may vary.

Other information

• Store at room temperature 15o to 30o C (59o to 86o F). • Active ingredients are micro-diluted in accordance with the Homeopathic Pharmacopoeia of the United States and are therefore non-toxic with no known side effects or contraindications.

Inactive ingredients

Copovidone, Crospovidone, Lactose, Magnesium stearate, Mannitol, Microcrystalline cellulose, Silicon dioxide, Sorbitol.

*THIS PRODUCT IS A HOMEOPATHIC REMEDY. AS SUCH, IT HAS NOT UNDERGONE REVIEW OR APPROVAL BY THE FDA AND THEREFORE HAS NOT BEEN DEMONSTRATED TO BE SAFE OR EFFECTIVE TO DIAGNOSE, TREAT, PREVENT, MITIGATE OR CURE ANY CONDITION OR DISEASE.

Questions or comments? 1-800-925-4733

DISTRIBUTED BY: WALGREEN CO.

200 WILMOT RD., DEERFIELD, IL 60015

100% SATISFACTION GUARANTEED

walgreens.com ©2022 Walgreen Co.